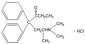 DRUG LABEL: Unknown
Manufacturer: Xanodyne Pharmaceuticals Inc.
Category: prescription | Type: HUMAN PRESCRIPTION DRUG LABELING
Date: 20071006
DEA Schedule: CII

METHADONE HYDROCHLORIDE INJECTION, USP

Rx only

CII

CONDITIONS FOR DISTRIBUTION AND USE

BOXED WARNING

CONDITIONS FOR DISTRIBUTION AND USE OF METHADONE PRODUCTS
FOR THE TREATMENT OF OPIOID ADDICTION

Code of Federal Regulations, Title 42, Sec 8

METHADONE PRODUCTS WHEN USED FOR THE TREATMENT OF OPIOID ADDICTION IN DETOXIFICATION OR MAINTENANCE PROGRAMS, SHALL BE DISPENSED ONLY BY OPIOID TREATMENT PROGRAMS (AND AGENCIES, PRACTITIONERS OR INSTITUTIONS BY FORMAL AGREEMENT WITH THE PROGRAM SPONSOR) CERTIFIED BY THE SUBSTANCE ABUSE AND MENTAL HEALTH SERVICES ADMINISTRATION AND APPROVED BY THE DESIGNATED STATE AUTHORITY. CERTIFIED TREATMENT PROGRAMS SHALL DISPENSE AND USE METHADONE IN ORAL FORM ONLY AND ACCORDING TO THE TREATMENT REQUIREMENTS STIPULATED IN THE FEDERAL OPIOID TREATMENT STANDARDS (42 CFR 8.12). See below for important regulatory exceptions to the general requirement for certification to provide opioid agonist treatment.

FAILURE TO ABIDE BY THE REQUIREMENTS IN THESE REGULATIONS MAY RESULT IN CRIMINAL PROSECUTION, SEIZURE OF THE DRUG SUPPLY, REVOCATION OF THE PROGRAM APPROVAL, AND INJUNCTION PRECLUDING OPERATION OF THE PROGRAM.

Regulatory Exceptions To The General Requirement For Certification To Provide Opioid Agonist Treatment:

1. During inpatient care, when the patient was admitted for any condition other than concurrent opioid addiction (pursuant to 21CFR 1306.07(c)), to facilitate the treatment of the primary admitting diagnosis). For patients unable to take oral medication, parenteral methadone may be used.
2. During an emergency period of no longer than 3 days while definitive care for the addiction is being sought in an appropriately licensed facility (pursuant to 21CFR 1306.07(b)).

DESCRIPTION

Methadone Hydrochloride Injection, USP, 10 mg/mL is an opioid analgesic.

Each milliliter of Methadone Hydrochloride Injection contains 10 mg (0.029 mmol) of methadone hydrochloride, equivalent to 8.95 mg of methadone free base.

Methadone hydrochloride is a white, crystalline material that is water-soluble.

Methadone hydrochloride is chemically described as 6-(dimethylamino)-4,4-diphenyl-3-hepatanone hydrochloride. Its molecular formula is C21H27NO•HCl and it has a molecular weight of 345.91. Methadone hydrochloride has a melting point of 235° C, and a pKa of 8.25 in water at 20°C. Its octanol/water partition coefficient at pH 7.4 is 117. A solution (1:100) in water has a pH between 4.5 and 6.5.

It has the following structural formula:

Methadone Hydrochloride Injection is a sterile injectable solution containing the following inactive ingredients: chlorobutanol, 0.5%, as a preservative, and sodium chloride. The pH of the sterile injectable solution may have been adjusted during manufacturing with sodium hydroxide and/or hydrochloric acid.

CLINICAL PHARMACOLOGY

Mechanism of Action

Methadone hydrochloride is a μ agonist; a synthetic opioid analgesic with multiple actions qualitatively similar to those of morphine, the most prominent of which involve the central nervous system and organs composed of smooth muscle. The principal therapeutic uses for methadone are for analgesia and for detoxification or maintenance in opioid addiction. The methadone abstinence syndrome, although qualitatively similar to that of morphine, differs in that the onset is slower, the course is more prolonged, and the symptoms are less severe. Some data also indicate that methadone acts as an antagonist at the N-methyl-D-aspartate (NMDA) receptor. The contribution of NMDA receptor antagonism to methadone's efficacy is unknown. Other NMDA receptor antagonists have been shown to produce neurotoxic effects in animals.

Pharmacokinetics

Absorption:

Methadone Hydrochloride Injection is intended for parenteral (intravenous, subcutaneous and intramuscular) administration. Methadone pharmacokinetics following subcutaneous and intramuscular administration have not been systematically studied and differences among the various parenteral routes have not been well characterized. As with many drugs, absorption into the systemic circulation may vary with subcutaneous and intramuscular administration.

Distribution:

Methadone is a lipophilic drug and the steady state volume of distribution ranges between 2 -6 L/kg. In plasma, methadone is predominantly bound to α1-acid glycoprotein (85% - 90%). Methadone is secreted in saliva, breast milk, amniotic fluid and umbilical cord plasma.

Metabolism:

Methadone is primarily metabolized by N-demethylation to an inactive metabolite, 2-ethylidene-1,5-dimethyl-3,3-diphenylpyrrolidene (EDDP). Cytochrome P450 enzymes, primarily CYP3A4 and to a lesser extent CYP2D6, are responsible for conversion of methadone to EDDP and other inactive metabolites, which are excreted mainly in urine.

Excretion:

Elimination of methadone is mediated by extensive biotransformation, followed by renal and fecal excretion. After single intravenous dose administration the plasma clearance of methadone ranged between 3-10 L/h and the terminal half-life (t½) ranged between 8 - 59 hours. Methadone has been known to persist in the liver and other tissues. Slow release from the liver and other tissues may prolong the duration of methadone action despite low plasma concentrations.

Pharmacokinetics in Special Populations:

Pregnancy

There are no pharmacokinetic studies of parenteral methadone in pregnancy. The disposition of oral methadone has been studied in approximately 30 pregnant patients in 2nd and 3rd trimesters. Elimination of methadone was significantly changed in pregnancy. Total body clearance of methadone was increased in pregnant patients compared to the same patients postpartum or to non-pregnant opioid-dependent women. The terminal half-life of methadone is decreased during second and third trimesters. The decrease in plasma half-life and increased clearance of methadone resulting in lower methadone trough levels during pregnancy can lead to withdrawal symptoms in some pregnant patients. The dosage may need to be increased or the dosing interval decreased in pregnant patients receiving methadone (See DOSAGE AND ADMINISTRATION).

Renal Impairment

Methadone pharmacokinetics have not been extensively evaluated in patients with renal insufficiency. Unchanged methadone and its metabolites are excreted in urine to a variable degree. Methadone is a basic (pKa=9.2) compound and the luminal pH of the urinary tract can affect its extraction from plasma. Urine acidification has been shown to increase renal elimination of methadone. Forced diuresis, peritoneal dialysis, hemodialysis, or charcoal hemoperfusion have not been established as beneficial for increasing methadone or metabolite elimination.

Hepatic Impairment

Methadone pharmacokinetics have not been extensively evaluated in patients with hepatic insufficiency. Methadone is metabolized in the liver and patients with liver impairment may be at risk of accumulating methadone after multiple dosing.

Gender

The pharmacokinetics of methadone have not been evaluated for gender specificity.

Race

The pharmacokinetics of methadone have not been evaluated for race specificity.

Geriatric

The pharmacokinetics of methadone have not been evaluated in geriatric population.

Pediatric

The pharmacokinetics of methadone have not been evaluated in pediatric population.

Drug Interactions

(see PRECAUTIONS, Drug Interactions)

Methadone undergoes hepatic N-demethylation by cytochrome P-450 isoforms, principally CYP3A4, and to a lesser extent CYP2D6. Coadministration of methadone with inducers of these enzymes may result in more rapid methadone metabolism and potentially, decreased effects of methadone. Conversely, administration with CYP3A4 or CYP2D6 inhibitors may reduce metabolism and potentiate methadone's effects. Therefore, drugs administered concomitantly with methadone should be evaluated for interaction potential (see Drug Interactions)

INDICATIONS AND USAGE

1. For the treatment of moderate to severe pain not responsive to non-narcotic analgesics.
2. For use in temporary treatment of opioid dependence in patients unable to take oral medication.

Outpatient maintenance and outpatient detoxification treatment may be provided only by opioid treatment programs (OTPs) certified by the Federal Substance Abuse and Mental Health Services Administration (SAMHSA) and registered by the Drug Enforcement Administration (DEA). This does not preclude the maintenance treatment of a patient with concurrent opioid addiction who is hospitalized for conditions other than opioid addiction and who requires temporary maintenance during the critical period of hospitalization, or of a patient whose enrollment has been verified in a program which has been certified for maintenance treatment with methadone.

NOTE: INJECTABLE METHADONE PRODUCTS ARE NOT APPROVED FOR THE OUTPATIENT TREATMENT OF OPIOID DEPENDENCE. IN THIS PATIENT POPULATION, PARENTERAL METHADONE IS TO BE USED ONLY FOR PATIENTS UNABLE TO TAKE ORAL MEDICATION, SUCH AS HOSPITALIZED PATIENTS.

CONTRAINDICATIONS

Methadone Hydrochloride Injection is contraindicated in patients with a known hypersensitivity to methadone hydrochloride or any other ingredient in Methadone Hydrochloride Injection. Methadone Hydrochloride Injection is contraindicated in any situation where opioids are contraindicated such as: patients with respiratory depression (in the absence of resuscitative equipment or in unmonitored settings), and in patients with acute bronchial asthma or hypercarbia.

WARNINGS

Cardiac Conduction Effects

BOXED WARNING

Laboratory studies, both in vivo and in vitro, have demonstrated that methadone inhibits cardiac potassium channels and prolongs the QT interval. Cases of QT interval prolongation and serious arrhythmia (torsades de pointes) have been observed during treatment with methadone. These cases appear to be more commonly associated with, but not limited to, higher dose treatment (> 200 mg/day). Most cases involve patients being treated for pain with large, multiple daily doses of methadone, although cases have been reported in patients receiving doses commonly used for maintenance treatment of opioid addiction.

Methadone should be administered with particular caution to patients already at risk for development of prolonged QT interval (e.g., cardiac hypertrophy, concomitant diuretic use, hypokalemia, hypomagnesemia). Careful monitoring is recommended when using methadone in patients with a history of cardiac conduction abnormalities, those taking medications affecting cardiac conduction, and in other cases where history or physical exam suggest an increased risk of dysrhythmia. QT prolongation has also been reported in patients with no prior cardiac history who have received high doses of methadone. Patients developing QT prolongation while on methadone treatment should be evaluated for the presence of modifiable risk factors, such as concomitant medications with cardiac effects, drugs which might cause electrolyte abnormalities, and drugs which might act as inhibitors of methadone metabolism. For use of methadone to treat pain, the risk of QT prolongation and development of dysrhythmias should be weighed against the benefit of adequate pain management and the availability of alternative therapies.

Methadone treatment for analgesic therapy in patients with acute or chronic pain should only be initiated if the potential analgesic or palliative care benefit of treatment with methadone has been considered to outweigh the risk of QT prolongation that has been reported with high doses of methadone.

The use of methadone in patients already known to have a prolonged QT interval has not been systematically studied.

In using methadone an individualized benefit to risk assessment should be carried out and should include evaluation of patient presentation and complete medical history. For patients judged to be at risk, careful monitoring of cardiovascular status, including QT prolongation and dysrhythmias and those described previously should be performed.

Respiratory Depression

Respiratory depression is the chief hazard from methadone hydrochloride. Respiratory depression is a particular potential problem in elderly or debilitated patients as well as in those suffering from conditions accompanied by hypoxia or hypercapnia when even moderate therapeutic doses may dangerously decrease pulmonary ventilation.

Methadone Hydrochloride Injection should be administered with extreme caution to patients with conditions accompanied by hypoxia, hypercapnia, or decreased respiratory reserve such as; asthma, chronic obstructive pulmonary disease or cor pulmonale, severe obesity, sleep apnea syndrome, myxedema, kyphoscoliosis, CNS depression or coma. In these patients even usual therapeutic doses of methadone may decrease respiratory drive while simultaneously increasing airway resistance to the point of apnea. Alternative non-opioid analgesics should be considered, and methadone should be employed only under careful medical supervision at the lowest effective dose.

Methadone's peak respiratory depressant effects typically occur later, and persist longer than its peak analgesic effects, in the short-term use setting. These characteristics can contribute to cases of iatrogenic overdose, particularly during treatment initiation and dose titration.

Incomplete Cross-Tolerance Between Methadone and Other Opioids

Patients tolerant to other opioids may be incompletely tolerant to methadone. Incomplete cross-tolerance is a particular concern for patients tolerant to other μ-opioid agonists when converting to methadone, making determination of dosing during opioid conversion complex. Deaths have been reported during conversion from chronic, high dose treatment with other opioid agonists. Therefore, it is critical to understand the pharmacokinetics of methadone when converting patients from other opioids (see DOSAGE AND ADMINISTRATION, Tables 1 and 2, for appropriate conversion schedules). A high degree of "opioid tolerance" does not eliminate the possibility of methadone toxicity.

Misuse, Abuse, and Diversion of Opioids

Methadone is a μ-agonist opioid with an abuse liability similar to that of morphine and is a Schedule II controlled substance. Methadone, like morphine and other opioids used for analgesia, has the potential for being abused and is subject to criminal diversion.

Methadone can be abused in a manner similar to other opioid agonists, legal or illicit. This should be considered when dispensing Methadone Hydrochloride Injection in situations where the clinician is concerned about an increased risk of misuse, abuse, or diversion.

Concerns about abuse, addiction, diversion should not prevent the proper management of pain.

Healthcare professionals should contact their State Professional Licensing Board, or State Controlled Substances Authority for information on how to prevent and detect abuse or diversion of this product.

Interactions with other CNS Depressants

Patients receiving other opioid analgesics, general anesthetics, phenothiazines, other tranquilizers, sedatives, hypnotics, or other CNS depressants (including alcohol) concomitantly with methadone may experience respiratory depression, hypotension, profound sedation, or coma (see PRECAUTIONS)

Interactions with Alcohol and Drugs of Abuse

Methadone may be expected to have additive effects when used in conjunction with alcohol, other opioids, or illicit drugs that cause central nervous system depression. Deaths associated with illicit use of methadone have frequently involved concomitant benzodiazepine abuse.

Head Injury and Increased Intracranial Pressure

The respiratory depressant effects of opioids and their capacity to elevate cerebrospinal-fluid pressure may be markedly exaggerated in the presence of head injury, other intracranial lesions or a pre-existing increase in intracranial pressure. Furthermore, opioids produce effects which may obscure the clinical course of patients with head injuries. In such patients, opioids must be used with caution, and only if it is deemed essential.

Acute Abdominal Conditions

The administration of opioids may obscure the diagnosis of clinical course of patients with acute abdominal conditions.

Hypotensive Effect

The administration of methadone may result in severe hypotension in patients whose ability to maintain normal blood pressure is compromised (i.e., severe volume depletion).

PRECAUTIONS

General

Methadone given on a fixed-dose schedule may have a narrow therapeutic index in certain patient populations, especially when combined with other drugs, and should be reserved for cases where the benefits of opioid analgesia outweigh the known potential risks of cardiac conduction abnormalities, respiratory depression, altered mental states and postural hypotension. Methadone Hydrochloride Injection should be used with caution in elderly and debilitated patients; patients who are known to be sensitive to central nervous system depressants, such as those with cardiovascular, pulmonary, renal, or hepatic disease; and in patients with comorbid conditions or concomitant medications which may predispose to dysrhythmia.

Selection of patients for treatment with methadone should be governed by the same principles that apply to the use of other parenteral opioids (see INDICATIONS AND USAGE). Physicians should individualize treatment in every case (see DOSAGE AND ADMINISTRATION), taking into account the high degree of interpatient variability in response to and metabolism of methadone.

Drug Interactions

In vitro results indicate that methadone undergoes hepatic N-demethylation by cytochrome P450 enzymes, principally CYP3A4, and to a lesser extent CYP2D6. Coadministration of methadone with inducers of these enzymes may result in a more rapid metabolism and potential for decreased effects of methadone, whereas administration with inhibitors may reduce metabolism and potentiate methadone's effects. Therefore, drugs administered concomitantly with methadone should be evaluated for interaction potential; clinicians are advised to evaluate individual response to drug therapy.

Opioid antagonists, mixed agonist/antagonists, and partial agonists: As with other μ-agonists, patients maintained on methadone may experience withdrawal symptoms when given these agents. Examples of such agents are naloxone, naltrexone, pentazocine, nalbuphine, butorphanol, and buprenorphine.

Anti-retroviral agents:

Nevirapine: Based on the known metabolism of methadone, nevirapine may decrease plasma concentrations of methadone by increasing its hepatic metabolism. Opioid withdrawal syndrome has been reported in patients treated with nevirapine and methadone concomitantly. Methadone-maintained patients beginning nevirapine therapy should be monitored for evidence of withdrawal and methadone dose should be adjusted accordingly.

Efavirenz: Coadministration of efavirenz in HIV-infected methadone-maintenance patients has resulted in decreased methadone plasma concentrations of methadone associated with signs of opiod withdrawal, and necessitating increases in methadone dose.

Ritonavir and Ritonavir/Lopinavir: Reduced plasma methadone levels have been observed after administration of ritonavir alone or ritonavir/lopinavir combination. Withdrawal symptoms were however, inconsistently observed. Caution is warranted when administering methadone to patients receiving ritonavir-containing regimens in addition to other drugs known to decrease methadone plasma levels.

Zidovudine: Experimental evidence suggests that methadone increases the area under the concentration-time curve (AUC) of zidovudine with possible toxic effects.

Didanosine and Stavudine: Experimental evidence suggests that methadone decreased the AUC and peak levels for didanosine and stavudine, with a more significant decrease for didanosine. Methadone disposition was not substantially altered.

Cytochrome P450 inducers: The following drug interactions were reported following coadministration of methadone with inducers of cytochrome P450 enzymes.

Rifampin: In patients well-stabilized on methadone, concomitant administration of rifampin resulted in marked reduction in serum methadone levels and concurrent appearance of withdrawal symptoms.

Phenytoin: In a pharmacokinetic study with patients on methadone maintenance therapy, phenytoin administration (250 mg b.i.d initially for 1 day followed by 300 mg QD for 3-4 days) resulted in ~50% reduction in methadone exposure and concurrently withdrawal symptoms occurred. Upon discontinuation of phenytoin, the incidence of withdrawal symptoms decreased and the methadone exposure increased and was comparable to pre-phenytoin dose scenario.

St. John's Wort, phenobarbital, carbamazepine: Administration of methadone along with other CYP3A4 inducers may result in withdrawal symptoms.

Cytochrome P450 inhibitors: Since the metabolism of methadone is mediated by the CYP3A4 isozyme, coadministration of drugs that inhibit CYP3A4 activity may cause decreased clearance of methadone. The expected clinical results would be increased or prolonged opioid effects. Thus patients coadministered with inhibitors of CYP3A4 such as azole antifungal agents (e.g., ketoconazole), macrolide antibiotics (e.g., erythromycin), while receiving methadone should be carefully monitored and dosage adjustment made if warranted. Some selective serotonin reuptake inhibitors (SSRI's) (i.e., sertraline, fluvoxamine) upon coadministration may increase methadone plasma levels and result in increased opiate effects or toxicity.

Others:

Monoamine Oxidase (MAO) Inhibitors: Therapeutic doses of meperidine have precipitated severe reactions in patients concurrently receiving monoamine oxidase inhibitors or those who have received such agents within 14 days. Similar reactions thus far have not been reported with methadone; but if the use of methadone is necessary in such patients, a sensitivity test should be performed in which repeated small incremental doses are administered over the course of several hours while the patient's condition and vital signs are under careful observation.

Desipramine: Blood levels of desipramine have increased with concurrent methadone therapy.

Potentially Arrhythmogenic Agents: Extreme caution is necessary when any drug known to have the potential to prolong the QT interval is prescribed in conjunction with methadone. Pharmacodynamic interactions may occur with concomitant use of methadone and potentially arrhythmogenic agents such as class I and III antiarrhythmics, some neuroleptics and tricyclic antidepressants, and calcium channel blockers. Caution should also be exercised when prescribing concomitant drugs capable of inducing electrolyte disturbances that may prolong the QT interval (hypomagnesemia, hypokalemia). These include diuretics, laxatives, and in rare cases mineralocorticoid hormones.

Interactions with other CNS Depressants: Patients receiving other opioid analgesics, general anesthetics, phenothiazines, other tranquilizers, sedatives, hypnotics, or other CNS depressants (including alcohol) concomitantly with methadone may experience respiratory depression, hypotension, profound sedation, or coma.

Use with Mixed Agonist/Antagonist Opioid Analgesics: Agonist/antagonist analgesics (i.e., pentazocine, nalbuphine, butorphanol, or buprenorphine) should not be administered to patients who have received or are receiving a course of therapy with a pure opioid agonist, such as Methadone Hydrochloride Injection. In this situation, mixed agonist/antagonist analgesics may reduce the analgesic effect of Methadone Hydrochloride Injection and/or may precipitate withdrawal symptoms.

Anxiety

Methadone, used by tolerant patients at a constant maintenance dosage, is not a tranquilizer. Patients who are maintained on this drug will react to life problems and stresses as do other individuals. Anxiety in a patient on methadone should not be confused with narcotic abstinence and should not prompt treatment by increasing the dosage of methadone. The action of methadone in maintenance treatment is limited to the control of symptoms of opioid dependence or pain. Methadone is ineffective for relief of general anxiety.

Acute Pain

Maintenance patients on a stable dose of methadone who experience physical trauma, postoperative pain or other causes of acute pain cannot be expected to derive analgesia from their stable dose of methadone regimens. Such patients should be given analgesics, including opioids, that would be indicated in other patients experiencing similar nociceptive stimulation. Due to the opioid tolerance induced by methadone, when opioids are required for management of acute pain in methadone patients, somewhat higher and/or more frequent doses will often be required than would be the case for other, non-tolerant patients.

Risk of Relapse in Patients on Methadone Maintenance Treatment of Opioid Addiction

Abrupt opioid discontinuation can lead to development of opioid withdrawal symptoms (see PRECAUTIONS). Presentation of these symptoms has been associated with an increased risk of susceptible patients to relapse to illicit drug use and should be considered when assessing the risks and benefit of methadone use.

Tolerance and Physical Dependence

Tolerance is the need for increasing doses of opioids to maintain a defined effect such as analgesia (in the absence of disease progression or other external factors). Physical dependence is manifested by withdrawal symptoms after abrupt discontinuation of a drug or upon administration of an antagonist. Physical dependence and/or tolerance are not unusual during chronic opioid therapy.

If methadone is abruptly discontinued in a physically dependent patient, an abstinence syndrome may occur. The opioid abstinence or withdrawal syndrome is characterized by some or all of the following: restlessness, lacrimation, rhinorrhea, yawning, perspiration, chills, myalgia, and mydriasis. Other symptoms also may develop, including: irritability, anxiety, backache, joint pain, weakness, abdominal cramps, insomnia, nausea, anorexia, vomiting, diarrhea, or increased blood pressure, respiratory rate, or heart rate.

In general, chronically administered methadone should not be abruptly discontinued.

Special-Risk Patients

Methadone should be given with caution and the initial dose reduced in certain patients, such as the elderly and debilitated and those with severe impairment of hepatic or renal function, hypothyroidism, Addison's disease, prostatic hypertrophy, or urethral stricture. The usual precautions appropriate to the use of parenteral opioids should be observed and the possibility of respiratory depression should always be kept in mind.

Information for Patients

Methadone, like all opioids, may impair the mental and/or physical abilities required for the performance of potentially hazardous tasks such as driving or operating machinery. The patient should be cautioned accordingly.

Methadone, like other opioids, may produce orthostatic hypotension in ambulatory patients.

Alcohol and other CNS depressants may produce an additive CNS depression, when taken with methadone, and should be avoided.

If a patient taking methadone experiences symptoms suggestive of an arrhythmia (such as palpitations, dizziness, lightheadedness, or syncope), that patient should seek immediate medical attention.

Carcinogenesis, Mutagenesis, Impairment of Fertility

Data from published reports of carcinogenicity studies indicate that there was a significant increase in pituitary adenomas in female B6C2F1 mice consuming 15 mg/kg/day methadone for two years. This dose was approximately 0.6 times a human daily oral dose of 120 mg/day, on a body surface area basis. However, this finding was not seen in mice consuming 60 mg/kg/day (approximately 2.5 times a human daily oral dose of 120 mg/day). Furthermore, in a two-year study of dietary administration of methadone to Fischer 344 rats, there was no clear evidence for treatment related increase in the incidence of neoplasms, at doses as high as 28 mg/kg/day in males and 88 mg/kg/day in females (approximately 2.3 times and 7.1 times, respectively, a human daily oral dose of 120 mg/day) based on body surface area comparison.

In published reports, methadone tested negative in tests for chromosome breakage and disjunction and sex-linked recessive lethal gene mutations in germ cells of Drosophila using feeding and injection procedures. Methadone treatment of male mice increased sex chromosome and autosome univalent chromosomes and translocations in multivalent chromosomes. Methadone tested positive in the E.coli DNA repair system and Neurospora crassa and mouse lymphoma forward mutation assays.

Pregnancy

TERATOGENIC EFFECTS

Teratogenic effects: Pregnancy Category C. There are no controlled studies of methadone use in pregnant women that can be used to establish safety. However, an expert review of published data on experiences with methadone use during pregnancy by TERIS - the Teratogen Information System -concluded that maternal use of methadone during pregnancy as part of a supervised, therapeutic regimen is unlikely to pose a substantial teratogenic risk (quantity and quality of data assessed as “limited to fair”), however, the data are insufficient to state that there is no risk (TERIS, last reviewed October, 2002). Pregnant women involved in methadone maintenance programs have been reported to have significantly improved prenatal care, improved fetal outcomes, and reduced mortality when compared to pregnant women using illicit drugs. Several factors complicate the interpretation of investigations of the children of women who took methadone during pregnancy. These include: the maternal use of illicit drugs, other maternal factors such as nutrition, infection, and psychosocial circumstances, limited information regarding dose and duration of methadone use during pregnancy, and the fact that most maternal exposure appears to occur after the first trimester of pregnancy. In addition, reported studies generally compare the benefit of methadone to the risk of untreated addiction to illicit drugs; the relevance of these findings to pain patients prescribed methadone during pregnancy is unclear.

Methadone has been detected in amniotic fluid and cord plasma at concentrations proportional to maternal plasma and in newborn urine at lower concentrations than corresponding maternal urine.

A retrospective series of 101 pregnant opiate-dependent women who underwent inpatient opiate detoxification with methadone did not demonstrate any increased risk of miscarriage in the 2nd trimester or premature delivery in the 3rd trimester.

Several studies have suggested that infants born to narcotic-addicted women treated with methadone during all or part of pregnancy have been found to have decreased fetal growth with reduced birth weight, length, and/or head circumference compared to controls. The growth deficit does not appear to persist into later childhood. However, children born to women treated with methadone during pregnancy have been shown to demonstrate mild but persistent deficits in performance on psychometric and behavioral tests.

Methadone should be used during pregnancy only if the potential benefit justifies the potential risk to the fetus.

Additional information on the potential risks of methadone may be derived from animal data. Methadone does not appear to be teratogenic in the rat or rabbit models. However, following large doses, methadone produced teratogenic effects in the guinea pig, hamster and mouse. One published study found that in hamster fetuses, subcutaneous methadone doses of 31 mg/kg or greater (estimated exposure was approximately 2 times a human daily oral dose of 120 mg/day on a mg/m^2 basis, or equivalent to a human daily intravenous dose of 120 mg/day) on day 8 of gestation produced exencephaly and neurological effects. Some of the reported effects were observed at doses that were maternally toxic. In another study, a single subcutaneous dose of 22-24 mg/kg methadone (estimated exposure was approximately equivalent to a human daily oral dose of 120 mg/day on a mg/m^2 basis; or half a human daily intravenous dose of 120 mg/day) on day 9 of gestation in mice also produced exencephaly in 11% of the embryos. However, no effects were reported in rats and rabbits at oral doses up to 40 mg/kg (estimated exposure was approximately 3 and 6 times, respectively, a human daily oral dose of 120 mg/day on a mg/m^2 basis; or 1.5 and 3 times a human daily intravenous dose of 120 mg/day) during days 6-15 and 6-18, respectively.

NONTERATOGENIC EFFECTS

Nonteratogenetic Effects: Babies born to mothers who have been taking opioids regularly prior to delivery may be physically dependent. Onset of withdrawal symptoms in infants is usually in the first days after birth but may be delayed for two to four weeks. Withdrawal signs in the newborn include irritability and excessive crying, tremors, hyperactive reflexes, increased respiratory rate, increased stools, sneezing, yawning, vomiting, and fever. The intensity of the syndrome does not always correlate with the duration of maternal opioid dose or maternal dose. There is no consensus on the appropriate management of infant withdrawal.

There are conflicting reports on whether the risk of sudden infant death syndrome (SIDS) is increased in infants born to women treated with methadone during pregnancy.

Abnormal fetal nonstress tests (NSTs) have been reported to occur more frequently when the test is performed 1-2 hours after a maintenance dose of methadone in late pregnancy compared to controls. Published animal studies suggest that perinatal exposure to opioids including methadone may alter neuronal development and behavior in the offspring. Perinatal methadone exposure in rats has been linked to alterations in learning ability, motor activity, thermal regulation, nociception responses and sensitivity to other drugs. Additional animal data demonstrates evidence for neurochemical changes in the brains of methadone-treated offspring, including the cholinergic, dopaminergic, noradrenergic and serotonergic systems.

Clinical Pharmacology for Pregnancy: Pregnant women have significantly lower trough plasma concentrations, increased plasma methadone clearance and shorter half-life than after delivery. Dosage adjustment using higher doses or administering the daily dose in divided doses may be necessary in pregnant women treated with methadone. [See CLINICAL PHARMACOLOGY and DOSAGE AND ADMINISTRATION].

Labor and Delivery: As with all opioids, administration of methadone to the mother shortly before delivery may result in some degree of respiratory depression in the newborn, especially if higher doses are used. Methadone is not recommended for obstetric analgesia because its long duration of action increases the probability of respiratory depression in the newborn. Narcotics with mixed agonist-antagonist properties should not be used for pain control during labor in patients chronically treated with methadone because they may precipitate acute withdrawal.

NURSING MOTHERS

Nursing mothers: Methadone is secreted into human milk. There is no information on use of parenteral methadone in breast feeding, or on the safety of the high doses of methadone typically used in chronic pain treatment. The safety of breastfeeding while taking oral methadone is also controversial. At maternal oral doses of 10-80 mg/day, methadone concentrations from 50 to 570 ug/L in milk have been reported, which, in the majority of samples, were lower than maternal serum drug concentrations at steady state. Peak methadone levels in milk occur approximately 4-5 hours after an oral dose. Based on an average milk consumption of 150 mL/kg/day, an infant would consume approximately 17.4 ug/kg/day, which is approximately 2-3% of the oral maternal dose. Methadone has been detected in very low plasma concentrations in some infants whose mothers were taking methadone. Women on high dose methadone maintenance, who are already breast feeding, should be counseled to wean breast-feeding gradually in order to prevent neonatal abstinence syndrome. Methadone-treated mothers considering nursing an opioid-naïve infant should be counseled of the presence of methadone in breast milk.

Because of the potential for serious adverse reactions in nursing infants from methadone, a decision should be made whether to discontinue nursing or to discontinue the drug, taking into account the importance of the drug to the mother.

Pediatric Use

Safety and effectiveness in pediatric patients below the age of 18 years have not been established.

Geriatric Use

Clinical studies of Methadone Hydrochloride Injection did not include sufficient numbers of subjects aged 65 and over to determine whether they respond differently from younger subjects. Other reported clinical experience has not identified differences in responses between the elderly and younger patients. In general, dose selection for elderly patients should be cautious, usually starting at the low end of the dosing range, reflecting the greater frequency of decreased hepatic, renal, or cardiac function and of concomitant disease or other drug therapy.

Renal Impairment

The use of methadone has not been extensively evaluated in patients with renal insufficiency.

Hepatic Impairment

The use of methadone has not been extensively evaluated in patients with hepatic insufficiency. Methadone is metabolized in the liver and patients with liver impairment may be at risk of accumulating methadone after multiple dosing.

Gender

The use of methadone has not been evaluated for gender specificity.

ADVERSE REACTIONS

Initial Administration: The initial methadone dose should be carefully titrated to the individual. Induction too rapid for the patient's sensitivity is more likely to produce adverse effects.

The major hazards of methadone are respiratory depression and, to a lesser degree, systemic hypotension. Respiratory arrest, shock, cardiac arrest, and death have occurred.

The most frequently observed adverse reactions include lightheadedness, dizziness, sedation, nausea, vomiting, and sweating. These effects seem to be more prominent in ambulatory patients and in those who are not suffering severe pain. In such individuals, lower doses of methadone are advisable.

Other adverse reactions that have been reported in patients (including opioid addicts taking methadone for detoxification or maintenance) receiving methadone include the following:

Body as a Whole: asthenia (weakness), edema, headache

Cardiovascular: Arrhythmias, bigeminal rhythms, bradycardia, extrasystoles, tachycardia, Torsade de Pointes, ventricular fibrillation, ventricular tachycardia. ECG abnormalities, prolonged QT interval, T-wave inversion, cardiomyopathy, flushing, heart failure, hypotension, palpitations, phlebitis, syncope.

Digestive: Abdominal pain, anorexia, biliary tract spasm, constipation, dry mouth, glossitis

Hematologic and Lymphatic: Reversible thrombocytopenia has been described in opioid addicts with chronic hepatitis.

Metabolic and Nutritional: Hypokalemia, hypomagnesemia, weight gain

Nervous: Agitation, confusion, seizures, disorientation, dysphoria, euphoria, insomnia

Respiratory: Pulmonary edema

Skin and appendages:

Intramuscular and Subcutaneous: Local tissue reactions (pain, erythema, swelling), particularly with continuous subcutaneous infusion

Intravenous: Pruritis, urticaria, other skin rashes, and rarely, hemorrhagic urticaria

Special senses: Visual disturbances

Urogenital: Antidiuretic effect, amenorrhea, urinary retention or hesitancy, reduced libido and/or potency

Maintenance on a Stabilized Dose: During prolonged administration of methadone, there is usually a gradual, yet progressive, disappearance of side effects over a period of several weeks. However, constipation and sweating often persist.

DRUG ABUSE AND DEPENDENCE

Methadone is a μ-agonist opioid with an abuse liability similar to that of morphine and is a Schedule II controlled substance. Methadone, like morphine and other opioids used for analgesia, has the potential for being abused and is subject to criminal diversion.

Abuse

Drug addiction is characterized by a preoccupation with the procurement, hoarding, and abuse of drugs for non-medicinal purposes. Drug addiction is treatable, utilizing a multi-disciplinary approach, but relapse is common.

“Drug seeking” behavior is very common to addicts and drug abusers. Drug seeking tactics include emergency calls or visits near the end of the office hours, refusal to undergo appropriate examination, testing or referral, repeated claims of loss of prescriptions, tampering with prescriptions and reluctance to provide prior medical records or contact information for other treating physician(s). Doctor shopping (visiting multiple prescribers) to obtain additional prescriptions is common among drug abusers and people suffering from untreated addictions.

Physical Dependence and Tolerance

Abuse and addiction are separate and distinct from physical dependence and tolerance. Physicians should be aware that addiction may not be accompanied by concurrent tolerance and symptoms of physical dependence in all addicts. In addition, abuse of opioids can occur in the absence of true addiction and is characterized by misuse for non-medical purposes, often in combination with other psychoactive substances. Methadone Hydrochloride Injection, like other opioids, may be diverted for non-medical use. Careful record-keeping of prescribing information, including quantity, frequency, and renewal requests is strongly advised.

Abuse of Methadone Hydrochloride Injection poses a risk of overdose and death. This risk is increased with concurrent abuse of Methadone Hydrochloride Injection with alcohol and other substances. In addition, parenteral drug abuse is commonly associated with transmission of infectious disease such as hepatitis and HIV.

Proper assessment of the patient, proper prescribing practices, periodic re-evaluation of therapy, and proper dispensing and storage are appropriate measures that help to limit abuse of opioid drugs.

Infants born to mothers physically dependent on opioids may also be physically dependent and may exhibit respiratory difficulties and withdrawal symptoms (See PRECAUTIONS; Pregnancy and Labor and Delivery)

OVERDOSAGE

Signs and Symptoms

Serious overdosage of methadone is characterized by respiratory depression (a decrease in respiratory rate and/or tidal volume, Cheyne-Stokes respiration, cyanosis), extreme somnolence progressing to stupor or coma, maximally constricted pupils, skeletal-muscle flaccidity, cold and clammy skin, and sometimes, bradycardia and hypotension. In severe overdosage, particularly by the intravenous route, apnea, circulatory collapse, cardiac arrest, and death may occur.

Treatment

Primary attention should be given to the reestablishment of adequate respiratory exchange through provision of a patent airway and institution of assisted or controlled ventilation. If a non-tolerant person takes a large dose of methadone, effective opioid antagonists are available to counteract the potentially lethal respiratory depression. The physician must remember, however, that methadone is a long-acting depressant (36 to 48 hours), whereas the antagonists act for much shorter periods (one to three hours). The patient must, therefore, be monitored continuously for recurrence of respiratory depression and may need to be treated repeatedly with the narcotic antagonist. If the diagnosis is correct and respiratory depression is due only to overdosage of methadone, the use of other respiratory stimulants is not indicated.

Opioid antagonists should not be administered in the absence of clinically significant respiratory or cardiovascular depression. In an individual physically dependent on opioids, the administration of the usual dose of an opioid antagonist may precipitate an acute withdrawal syndrome. The severity of this syndrome will depend on the degree of physical dependence and the dose of the antagonist administered. If antagonists must be used to treat serious respiratory depression in the physically dependent patient, the antagonist should be administered with extreme care and by titration with smaller than usual doses of the antagonist.

Intravenously administered naloxone or nalmefene may be used to reverse signs of intoxication. Because of the relatively short half-life of naloxone as compared with methadone, repeated injections may be required until the status of the patient remains satisfactory. Naloxone may also be administered by continuous intravenous infusion.

Oxygen, intravenous fluids, vasopressors, and other supportive measures should be employed as indicated.

DOSAGE AND ADMINISTRATION

Methadone differs from many other opioid agonists in several important ways. Methadone's pharmacokinetic properties, coupled with high interpatient variability in its absorption, metabolism, and relative analgesic potency, necessitate a cautious and highly individualized approach to prescribing. Particular vigilance is necessary during treatment initiation, during conversion from one opioid to another, and during dose titration.

While methadone's duration of analgesic action (typically 4 to 8 hours) in the setting of single-dose studies approximates that of morphine, methadone's plasma elimination half-life is substantially longer than that of morphine (typically 8 to 59 hours vs. 1 to 5 hours). Methadone's peak respiratory depressant effects typically occur later, and persist longer than its peak analgesic effects. Also, with repeated dosing, methadone may be retained in the liver and then slowly released, prolonging the duration of action despite low plasma concentrations. For these reasons, steady-state plasma concentrations, and full analgesic effects, are usually not attained until 3 to 5 days of dosing. Additionally, incomplete cross-tolerance between μ-opioid agonists makes determination of dosing during opioid conversion complex.

All of these characteristics make methadone dosing complex and can contribute to cases of iatrogenic overdose, particularly during treatment initiation and dose titration. A high degree of "opioid tolerance" does not eliminate the possibility of methadone overdose, iatrogenic or otherwise. Deaths have been reported during conversion to methadone from chronic, high-dose treatment with other opioid agonists.

Treatment of Pain

Optimal methadone initiation and dose titration strategies for the treatment of pain have not been determined. Published equianalgesic conversion ratios between methadone and other opioids are imprecise, providing at best, only population averages that cannot be applied consistently to all patients. It should be noted that many commonly cited equianalgesia tables only present relative analgesic potencies of single opioid doses in non-tolerant patients, thus greatly underestimating methadone's analgesic potency, and its potential for adverse effects in repeated-dose settings. Regardless of the dose determination strategy employed, methadone is most safely initiated and titrated using small initial doses and gradual dose adjustments.

As with all opioid drugs, it is necessary to adjust the dosing regimen for each patient individually, taking into account the patient's prior analgesic treatment experience. The following dosing recommendations should only be considered as suggested approaches to what is actually a series of clinical decisions over time in the management of the pain of each individual patient. Prescribers should always follow appropriate pain management principles of careful assessment and ongoing monitoring.

In the selection of an initial dose of Methadone Hydrochloride Injection, attention should be given to the following:

1. The total daily dose, potency and specific characteristics of the opioid the patient had been taking previously, if any;
2. The relative potency estimate used to calculate an equianalgesic starting methadone dose, in particular, whether it is intended for use in acute or chronic methadone dosing;
3. The patient's degree of opioid tolerance;
4. The age, general condition and medical status of the patient;
5. Concurrent medications, particularly other CNS and respiratory depressants;
6. The type, severity and expected duration of the patient's pain;
7. The acceptable balance between pain control and adverse side effects.

Methadone Hydrochloride Injection may be administered intravenously, subcutaneously or intramuscularly. The absorption of subcutaneous and intramuscular methadone has not been well characterized and appears to be unpredictable. Local tissue reactions may occur.

Parenteral products should be inspected visually for particulate matter and discoloration prior to administration, whenever solution and container permit.

Initiation of Therapy in Opioid Non-Tolerant Patients

When parenteral methadone is used as the first analgesic in patients who are not already being treated with, and tolerant to, opioids, the usual intravenous methadone starting dose is 2.5 mg to 10 mg every 8 to 12 hours, slowly titrated to effect. More frequent administration may be required during methadone initiation in order to maintain adequate analgesia, and extreme caution is necessary to avoid overdosage, taking into account methadone's long elimination half life.

Conversion from oral methadone to parenteral methadone should initially use a 2:1 dose ratio (e.g., 10 mg oral methadone to 5 mg parenteral methadone).

Switching Patients to Parenteral Methadone from other Chronic Opioids

Switching a patient from another chronically administered opioid to methadone requires caution due to the uncertainty of dose conversion ratios and incomplete cross-tolerance. Deaths have occurred in opioid tolerant patients during conversion to methadone.

Conversion ratios in many commonly used equianalgesic dosing tables do not apply in the setting of repeated methadone dosing. Although with single-dose administration the onset and duration of analgesic action, as well as the analgesic potency of methadone and morphine, are similar methadone's potency increases over time with repeated dosing. Furthermore, the conversion ratio between methadone and other opiates varies dramatically depending on baseline opiate (morphine equivalent) use as shown in the table below.

The dose conversion scheme below is derived from various consensus guidelines for converting chronic pain patients to methadone from morphine. The guidelines used to construct this table, however, were all designed for converting patients from oral morphine to oral methadone. The third column assumes a 2:1 ratio for converting from oral to intravenous methadone. Clinicians should consult published conversion guidelines to determine the equivalent morphine dose for patients converting from other opioids.

Table 1. Oral Morphine to Intravenous Methadone Conversion for Chronic Administration
Total Daily Baseline Oral | Estimated Daily Oral Methadone | Estimated Daily Intravenous
Morphine Dose | Reguirement as Percent of | Methadone as Percent of Total Daily
 | Total Daily Morphine Dose | Oral Morphine Dose*
< 100mg | 20% to 30% | 10% to 15%
100 to 300 mg | 10% to 20% | 5% to 10%
300 to 600 mg | 8% to 12% | 4% to 6%
600 mg to 1000 mg | 5% to 10% | 3% to 5%
> 1000 mg | < 5% | < 3%
*The total daily methadone dose derived from the table above may then be divided to reflect the intended dosing schedule (i.e., for administration every 8 hours, divide total daily methadone dose by 3).

Table 2. Parenteral Morphine to Intravenous Methadone Conversion for Chronic Administration (Derived from Table 1, assuming a 3:1 oral:parenteral morphine ratio)
Total Daily Baseline Parenteral | Estimated Daily Parenteral Methadone
Morphine Dose | Requirement as Percent of Total Daily Morphine Dose*
10 mg to 30 mg | 40% to 66%
30 mg to 50 mg | 27% to 66%
50 mg to 100 mg | 22% to 50%
100 mg to 200 mg | 15% to 34%
200 mg to 500 mg | 10% to 20%
*The total daily methadone dose derived from the table above may then be divided to reflect the intended dosing schedule (i.e., for administration every 8 hours, divide total daily methadone dose by 3).

Note: Equianalgesic methadone dosing varies not only between patients, but also within the same patient, depending on baseline morphine (or other opioid) dose. Tables 1 and 2 have been included in order to illustrate this concept and to provide a safe starting point for opioid conversion. Methadone dosing should not be based solely on these tables. Methadone conversion and dose titration methods should always be individualized to account for the patient's prior opioid exposure, general medical condition, concomitant medication, and anticipated breakthrough medication use. The endpoint of titration is achievement of adequate pain relief, balanced against tolerability of opioid side effects. If a patient develops intolerable opioid related side effects, the methadone dose, or dosing interval, may need to be decreased.

Methadone conversion and dose titration methods should always be individualized to account for the patient's prior opioid exposure, general medical condition, concomitant medication, and anticipated breakthrough medication use. The endpoint of titration is achievement of adequate pain relief, balanced against tolerability of opioid side effects. If a patient develops intolerable opioid related side effects, the methadone dose, or dosing interval, may need to be decreased.

Dosage Adjustment During Pregnancy

Methadone clearance may be increased during pregnancy. Several small studies have demonstrated significantly lower trough methadone plasma concentrations and shorter methadone half-lives in women during their pregnancy compared to after their delivery. During pregnancy a woman's methadone dose may need to be increased, or their dosing interval decreased. Methadone should be used in pregnancy only if the potential benefit justifies the potential risk to the fetus.

Detoxification and Maintenance Treatment of Opiate Dependence

For detoxification and maintenance of opiate dependence, methadone should be administered in accordance with the treatment standards cited in 42CFR Section 8.12, including limitations on unsupervised administration. Injectable methadone products are not approved for the outpatient treatment of opioid dependence. Parenteral methadone should be used only for patients who are unable to take oral medication, such as during hospitalization. The patient's oral methadone dose should be converted to an equivalent parenteral dose using the considerations above.

HOW SUPPLIED

Multiple-Dose Vials: 10 mg/mL, 20 mL, NDC 66479-530-02

One vial per package

Protect from light. Store in carton until contents have been used.

Store at 25°C (77°F); excursions are permitted to 15°-30°C (59°-86°F) [See USP Controlled Room Temperature]

Manufactured by: AAIPharma Inc., Charleston, SC 29405

Marketed by: Xanodyne Pharmaceuticals Inc., Newport, KY 41071

Xanodyne®

Pharmaceuticals, inc.

©2006, Xanodyne Pharmaceuticals Inc. PC3374B Rev. 03-2006